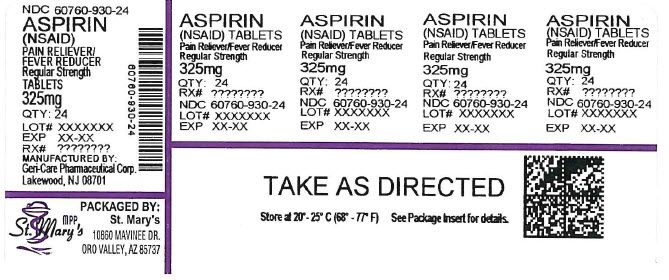 DRUG LABEL: Aspirin
NDC: 60760-930 | Form: TABLET
Manufacturer: ST. MARY'S MEDICAL PARK PHARMACY
Category: otc | Type: HUMAN OTC DRUG LABEL
Date: 20260127

ACTIVE INGREDIENTS: ASPIRIN 325 mg/1 1
INACTIVE INGREDIENTS: STARCH, CORN

Geri Care 44-249

Active ingredient (in each tablet)

Aspirin 325 mg (NSAID)*
*nonsteroidal anti-inflammatory drug

Purpose

Pain reliever/fever reducer

Uses

temporarily relieves:

- pain and fever of colds
- headache
- muscle pain
- minor pain of arthritis
- toothache
- menstrual pain

Warnings

Reye's syndrome:Children and teenagers who have or are recovering from chicken pox or flu-like symptoms should not use this product. When using this product, if changes in behavior with nausea and vomiting occur, consult a doctor because these symptoms could be an early sign of Reye's syndrome, a rare but serious illness.

Allergy alert:Aspirin may cause a severe allergic reaction, which may include:

- facial swelling
- shock
- hives
- asthma (wheezing)

Stomach bleeding warning:This product contains an NSAID, which may cause severe stomach bleeding. The chance is higher if you

- are age 60 or older
- take other drugs containing prescription or nonprescription NSAIDs [aspirin, ibuprofen, naproxen, or others]
- have 3 or more alcoholic drinks every day while using this product
- take more or for a longer time than directed
- have had stomach ulcers or bleeding problems
- take a blood thinning (anticoagulant) or steroid drug

Do not use

- if you are allergic to aspirin or any other pain reliever/fever reducer
- if you have ever had an allergic reaction to this product or any of its ingredients

Ask a doctor before use if

- you have asthma
- stomach bleeding warning applies to you
- you have a history of stomach problems, such as heartburn
- you have high blood pressure, heart disease, liver cirrhosis, or kidney disease
- you are taking a diuretic

Ask a doctor or pharmacist before use if you are

taking a prescription drug for

- gout
- diabetes
- arthritis

Stop use and ask a doctor if

- an allergic reaction occurs. Seek medical help right away.
- you experience any of the following signs of stomach bleeding:
  - vomit blood
  - have bloody or black stools
  - have stomach pain that does not get better
  - feel faint
- ringing in the ears or a loss of hearing occurs
- pain gets worse or lasts more than 10 days
- fever gets worse or lasts more than 3 days
- redness or swelling is present
- new symptoms occur

These could be signs of a serious condition.

If pregnant or breast-feeding,

ask a health professional before use. It is especially important not to use aspirin at 20 weeks or later in pregnancy unless definitely directed to do so by a doctor because it may cause problems in the unborn child or complications during delivery.

Keep out of reach of children.

In case of overdose, get medical help or contact a Poison Control Center right away.

Directions

- do not take more than directed
- drink a full glass of water with each dose
- adults and children 12 years and over: take 1 or 2 tablets every 4 hours or 3 tablets every 6 hours not to exceed 12 tablets in 24 hours unless directed by a doctor
- children under 12 years: do not use unless directed by a doctor

Other information

- use by expiration date on package
- store at 25ºC (77ºF); excursions permitted between 15º-30ºC (59º-86ºF)

Inactive ingredient

corn starch

Questions or comments?

1-800-540-3765